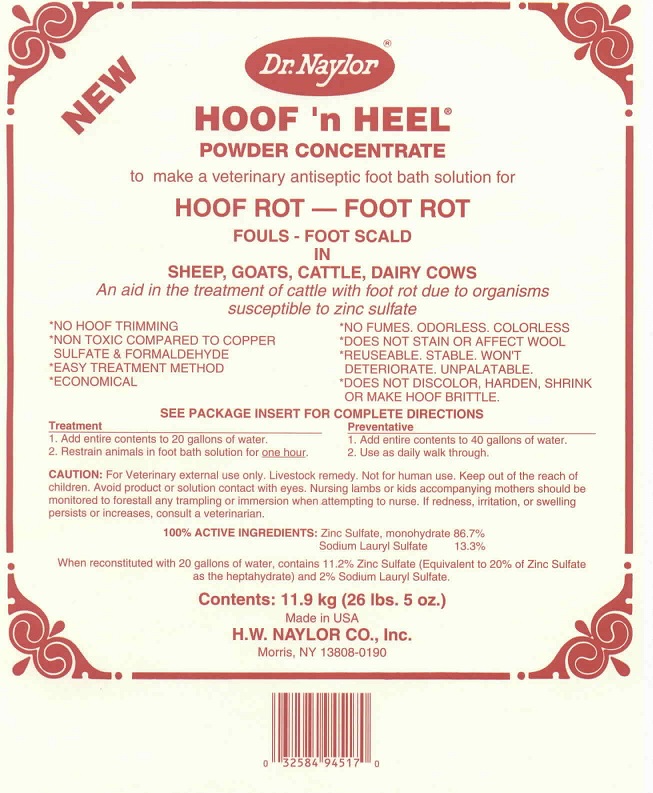 DRUG LABEL: HOOF n HEEL 
NDC: 15878-514 | Form: CONCENTRATE
Manufacturer: H. W. Naylor Company Inc.
Category: animal | Type: OTC ANIMAL DRUG LABEL
Date: 20211208

ACTIVE INGREDIENTS: Zinc Sulfate 1 kg/1 kg; Sodium Lauryl Sulfate .018 kg/1 kg

HOOF 'n HEEL®
POWDER CONCENTRATE

Active Ingredients

100% ACTIVE INGREDIENTS: Zinc Sulfate, monohydrate 86.7%
Sodium Lauryl Sulfate 13.3%
When reconstituted with 20 gallons of water, contains 11.2% Zinc Sulfate (Equivalent to 20% Zinc Sulfate as the heptahydrate) and 2% Sodium Lauryl Sulfate

Purpose

An aid in the treatment of cattle with foot rot due to organisms susceptible to zinc sulfate.

Directions

Treatment
1. Add entire contents to 20 gallons of water.
2. Restrain animals in foot bath solution for one hour.

Preventative
1. Add entire contents to 40 gallons of water.
2. Use as daily walk through.

CAUTION:

For Veterinary external use only. Livestock remedy. Not for human use. Avoid product or solution contact with eyes. Nursing lambs or kids accompanying mothers should be monitored to forestall any trampling or immersion when attempting to nurse. If redness, irritations, or swelling persists or increases, consult a veterinarian.

Keep out of the reach of children.

Other Ingredients

Add water for reconstitution

Questions?

www.drnaylor.com

Principal Display Panel

NEW
Dr. Naylor®
HOOF 'n HEEL®
POWDER CONCENTRATE
HOOF ROT — FOOT ROT
FOULS - FOOT SCALD
IN SHEEP, GOATS, CATTLE, DAIRY COWS
An aid in the treatment of cattle with foot rot due to organisms susceptible to zinc sulfate.
*NO HOOF TRIMMING
*NON TOXIC COMPARED TO COPPER SULFATE & FORMALDEHYDE
*EASY TREATMENT METHOD*ECONOMICAL
*NO FUMES. ODORLESS. COLORLESS
*DOES NOT STAIN OR AFFECT WOOL*REUSEABLE. STABLE. WON'T DETERIORATE. UNPALATABLE.
*DOES NOT DISCOLOR, HARDEN, SHRINK OR MAKE HOOF BRITTLE
SEE PACKAGE INSERT FOR COMPLETE DIRECTIONS
Contents: 11.9 kg (26 lbs. 5 oz.)
Made in U.S.A.
H.W. NAYLOR CO., Inc.
Morris NY 13808-0190